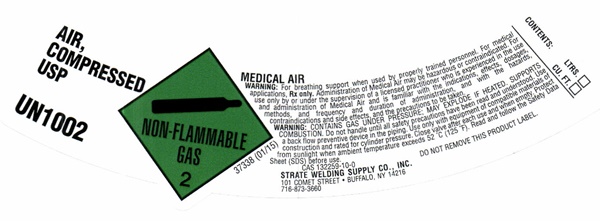 DRUG LABEL: MEDICAL AIR
NDC: 49221-0025 | Form: GAS
Manufacturer: Strate Welding Supply Co., Inc.
Category: prescription | Type: HUMAN PRESCRIPTION DRUG LABEL
Date: 20241028

ACTIVE INGREDIENTS: OXYGEN 21 L/100 L
INACTIVE INGREDIENTS: NITROGEN

MEDICAL AIR - 0025

AIR COMPRESSED USP LABEL

LINDE AIR, COMPRESSED UN 1002 DO NOT REMOVE THIS LABEL L AND SP 7061E MG 812H 11/07 MADE IN USA NON-FLAMMABLE 2

MEDICAL AIR, U.S.P.

CAUTION: HIGH PRESSURE GAS MAY ACCELERATE COMBUSTION.

KEEP OIL AND GREASE AWAY. USE ONLY WITH EQUIPMENT DESIGNED FOR COMPRESSED AIR SERVICE AND RATED FOR CYLINDER PRESSURE. USER SHALL SECURE CYLINDER IN USE AND IN STORAGE. USE IN UPRIGHT POSITION. CLOSE VALVE AFTER EACH USE AND WHEN EMPTY. KEEP VALVE PROTECTIVE CAP IN PLACE WHEN NOT IN USE, IF SO EQUIPPED.USE IN ACCORDANCE WITH THE SPECIFIC MATERIAL SAFETY DATA SHEET (MSDS) FOR THIS PRODUCT. WWW.LINDEUS.COM

WARNING: FOR BREATHING SUPPORT WHEN USED BY PROPERLY TRAINED PERSONNEL. FOR MEDICAL APPLICATIONS Rx ONLY. ADMINISTRATION OF MEDICAL AIR MAY BE HAZARDOUS OR CONTRAINDICATED. FOR MEDICAL USE ONLY BY OR UNDER THE SUPERVISION OF A LICENSED PRACTITIONER WHO IS EXPERIENCED IN THE USE AND ADMINISTRATION OF MEDICAL AIR USP AND IS FAMILIAR WITH THE INDICATIONS, EFFECTS, DOSAGES, METHODS, AND FREQUENCY AND DURATION OF ADMINISTRATION, AND WITH THE HAZARDS, CONTRAINDICATIONS AND SIDE EFFECTS AND PRECAUTIONS TO BE TAKEN.

TO BE FILLED BY A LINDE AUTHORIZED FACILITY ONLY. RETURN WITH 25 PSIG.

STRATE WELDING SUPPLY CO., INC. 101 COMET STREET BUFFALO, NY 14216

PRESSURE: PSIG AT 70 DEGREES F

SIZE LITERS CONTENTS